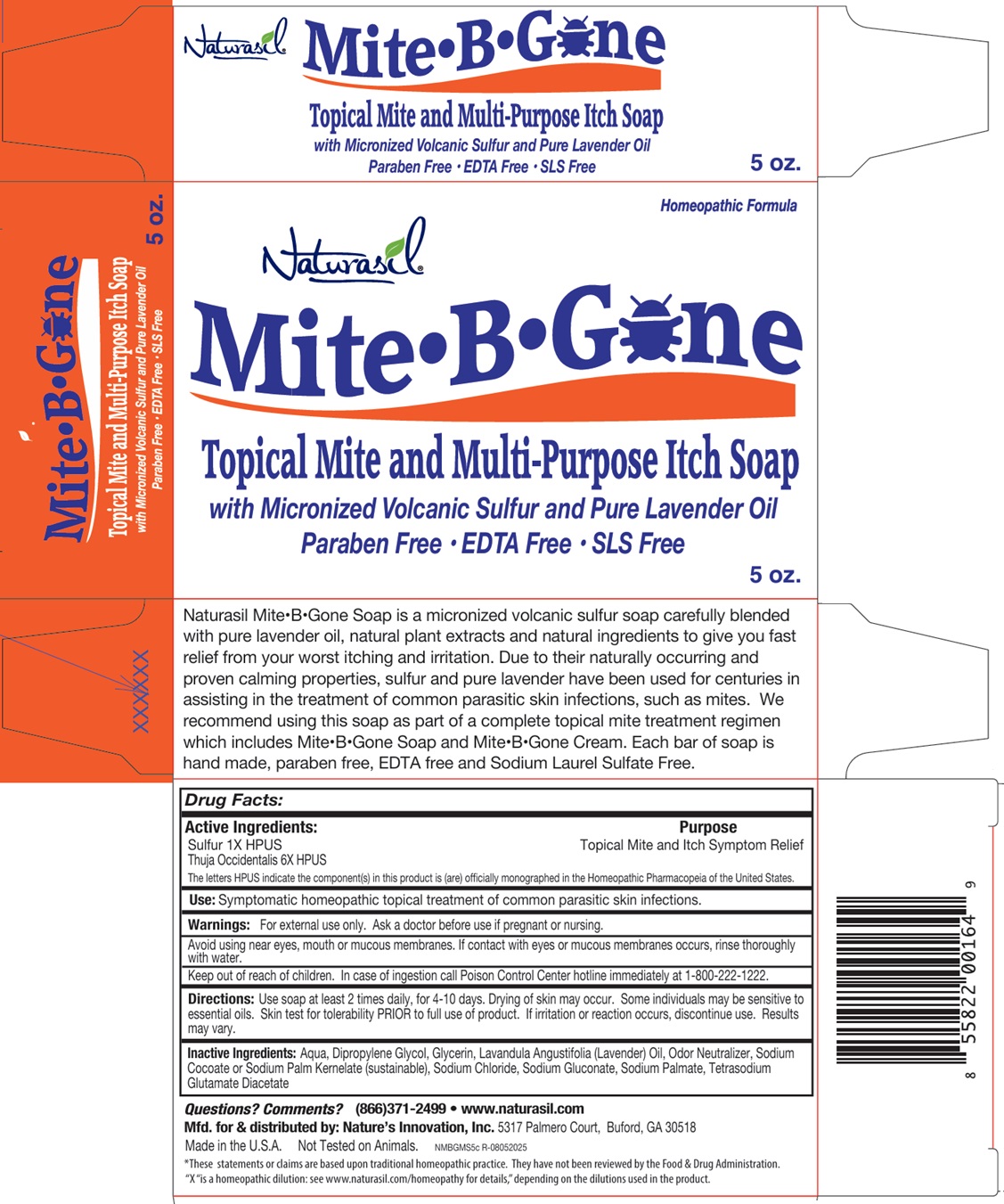 DRUG LABEL: Naturasil Mite B Gone
NDC: 10893-661 | Form: SOAP
Manufacturer: Nature's Innovation, Inc.
Category: homeopathic | Type: HUMAN OTC DRUG LABEL
Date: 20251107

ACTIVE INGREDIENTS: SULFUR 1 [hp_X]/1 g; THUJA OCCIDENTALIS LEAF 6 [hp_X]/1 g
INACTIVE INGREDIENTS: WATER; DIPROPYLENE GLYCOL; GLYCERIN; LAVENDER OIL; SODIUM COCOATE; SODIUM PALM KERNELATE; SODIUM CHLORIDE; SODIUM GLUCONATE; SODIUM PALMATE; TETRASODIUM GLUTAMATE DIACETATE

Naturasil Mite•B•Gone Soap

Active Ingredients:

Sulfur 1X HPUS,
Thuja Occidentalis 6X HPUS

The letters HPUS indicate the component(s) in this product is (are) officially monographed in the Homeopathic Pharmacopeia of the United States.

Purpose

Topical Mite and Itch Symptom Relief

Use:

Symptomatic homeopathic topical treatment of common parasitic skin infections.

Warnings:

For external use only. Ask a doctor before use if pregnant or nursing.

Avoid using near eyes, mouth or mucous membranes. If contact with eyes or mucous membranes occurs, rinse thoroughly with water.

Keep out of reach of children. In case of ingestion, call Poison Control Center hotline immediately at 1-800-222-1222.

Directions:

Use soap at least 2 times daily, for 4-10 days. Drying of skin may occur. Some individuals may be sensitive to essential oils. Skin test for tolerability PRIOR to full use of product. If irritation or reaction occurs, discontinue use. Results may vary.

Inactive Ingredients:

Aqua, Dipropylene Glycol, Glycerin, Lavandula Angustifolia (Lavender) Oil, Odor Neutralizer, Sodium Cocoate or Sodium Palm Kernelate (sustainable), Sodium Chloride, Sodium Gluconate, Sodium Palmate, Tetrasodium Glutamate Diacetate

Questions? Comments?

(866)371-2499 • www.naturasil.com

Homeopathic Formula

Topical Mite and Multi-Purpose Itch Soap

with Micronized Volcanic Sulfur and Pure Lavender Oil,

Paraben Free • EDTA Free • SLS Free

Naturasil Mite•B•Gone Soap is a micronized volcanic sulfur soap carefully blended with pure lavender oil, natural plant extracts and natural ingredients to give you fast relief from your worst itching and irritation. Due to their naturally occurring and proven calming properties, sulfur and pure lavender have been used for centuries in assisting in the treatment of common parasitic skin infections, such as mites. We recommend using this soap as part of a complete topical mite treatment regimen which includes Mite•B•Gone Soap and Mite•B•Gone Cream. Each bar of soap is hand made, paraben free, EDTA free and Sodium Laurel Sulfate Free.

Mfd. for & distributed by: Nature’s Innovation, Inc. 5317 Palmero Court, Buford, GA 30518

Made in the U.S.A. Not Tested on Animals.

*These statements or claims are based upon traditional homeopathic practice. They have not been reviewed by the Food & Drug Administration. “X“ is a homeopathic dilution: see www.naturasil.com/homeopathy for details," depending on the dilutions used in the product.